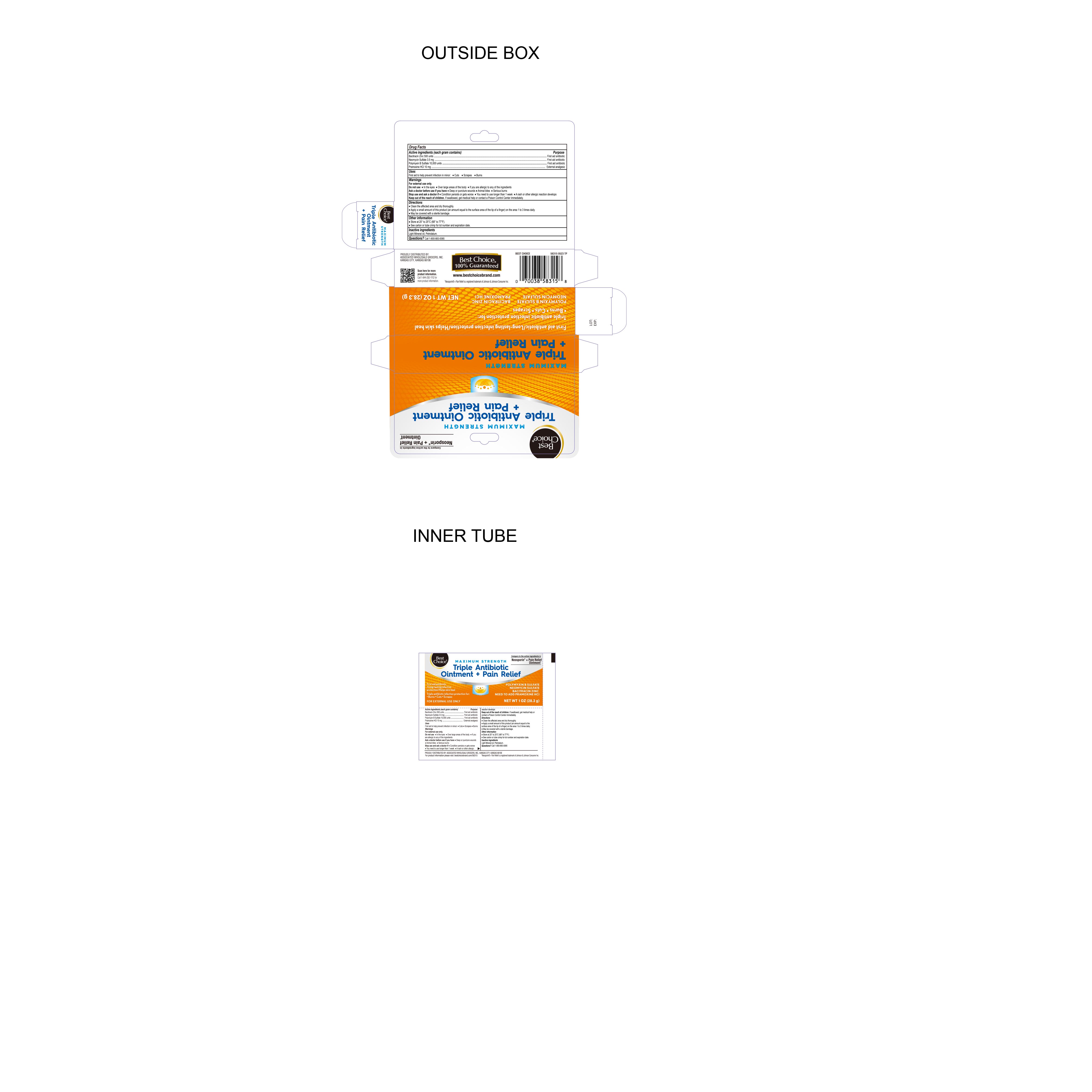 DRUG LABEL: Triple Antibiotic and Pain Relief
NDC: 69396-132 | Form: OINTMENT
Manufacturer: Trifecta Pharmaceutical USA LLC
Category: otc | Type: HUMAN OTC DRUG LABEL
Date: 20241231

ACTIVE INGREDIENTS: BACITRACIN ZINC 500 [USP'U]/100 g; NEOMYCIN SULFATE 3.5 mg/100 g; PRAMOXINE HYDROCHLORIDE 10 mg/100 g; POLYMYXIN B SULFATE 10000 [USP'U]/100 g
INACTIVE INGREDIENTS: PETROLATUM; LIGHT MINERAL OIL

Best Choice Triple Antibiotic Ointment + Pain Relief

Active Ingredient

Bacitracin zinc 500 Units

Purpose

First Aid Antibiotic

Active Ingredient

Neomycin Sulfate 3.5mg

Purpose

First Aid Antibiotic

Active Ingredient

Polymyxin B Sulfate10,000 Units

Purpose

First Aid Antibiotic

Active Ingredient

Pramoxine HCL 10mg

Purpose

External Analgesic

Uses

First Aid to help prevent infection in minor:

- Cuts
- Scrapes
- Burns

Warnings

For external use only. Do not use:

- In eyes
- Over large areas of the body
- If you are allergic to any of the ingredients

Ask a Doctor before Use

Ask Doctor before use if you have:

- Deep or puncture wounds
- Animal bites
- Serious burns

Stop Use and ask a Doctor if:

- Condition persists or gets worse
- You need to use longer than 1 week
- A rash or other allergic reaction develops

Keep out of Reach of Children

If Swallowed, get medical help or contact a Poison Control Center immediately

Directions

- Clean the affected area and dry thoroughly
- Apply a small amount of this product (an amount equal to the surface area of the tip of a finger) on the area 1 to 3 times daily
- May be covered with a sterile bandage

Other Information

- Store at 20° to 25°C (68° to 77°F)
- See carton or tube crimp for lot number and expiration date

Inactive Ingredient:

Light Mineral Oil, Petrolatum

Questions?

Call 1-800-883-0085

PROUDLY DISTRIBUTED BY: ASSOCIATED WHOLESALE GROCERS, INC.

KANSAS CITY, KANSAS 66106

For product information please visit: bestchoicebrand.com/58315

*Neosporin® + Pain Reliefis a registered trademark of Johnson & Johnson Consumer Inc.